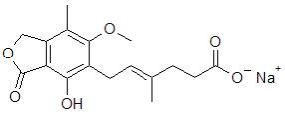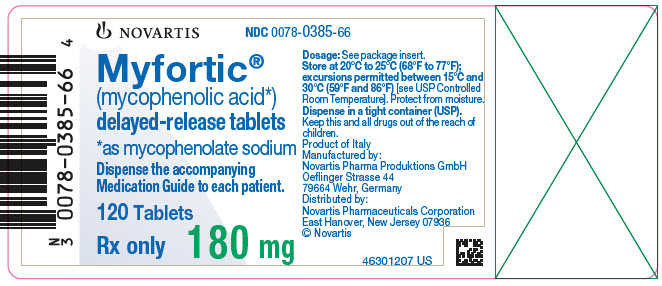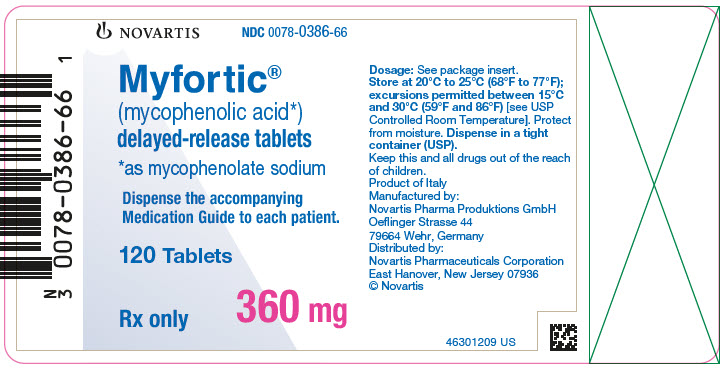 DRUG LABEL: Myfortic
NDC: 0078-0386 | Form: TABLET, DELAYED RELEASE
Manufacturer: Novartis Pharmaceuticals Corporation
Category: prescription | Type: HUMAN PRESCRIPTION DRUG LABEL
Date: 20251209

ACTIVE INGREDIENTS: MYCOPHENOLATE SODIUM 360 mg/1 1
INACTIVE INGREDIENTS: SILICON DIOXIDE; CROSPOVIDONE; HYPROMELLOSES; FERRIC OXIDE RED; FERRIC OXIDE YELLOW; ANHYDROUS LACTOSE; MAGNESIUM STEARATE; POVIDONE K30; STARCH, CORN; TITANIUM DIOXIDE

HIGHLIGHTS OF PRESCRIBING INFORMATION

These highlights do not include all the information needed to use MYFORTIC safely and effectively. See full prescribing information for MYFORTIC.
MYFORTIC® (mycophenolic acid) delayed-release tablets, for oral use
Initial U.S. Approval: 2004

RECENT MAJOR CHANGES

Warnings and Precautions, Hypersensitivity Reaction (5.9) | 6/2025

WARNING: EMBRYO-FETAL TOXICITY, MALIGNANCIES, AND SERIOUS INFECTIONS

See full prescribing information for complete boxed warning

- Use during pregnancy is associated with increased risks of pregnancy loss and congenital malformations. Avoid if safer treatment options are available. Females of reproductive potential must be counseled regarding pregnancy prevention and planning. (5.1, 8.1, 8.3)
- Only physicians experienced in immunosuppressive therapy and management of organ transplant patients should prescribe Myfortic. (5.2)
- Increased risk of development of lymphoma and other malignancies, particularly of the skin, due to immunosuppression. (5.3)
- Increased susceptibility to bacterial, viral, fungal, and protozoal infections, including opportunistic infections. (5.4, 5.5)

1 INDICATIONS AND USAGE

- Myfortic is an antimetabolite immunosuppressant indicated for prophylaxis of organ rejection in adult patients receiving kidney transplants and in pediatric patients at least 5 years of age and older who are at least 6 months post kidney transplant. (1.1)
- Use in combination with cyclosporine and corticosteroids. (1.1)

Limitations of Use:

- Myfortic delayed-release tablets and mycophenolate mofetil tablets and capsules should not be used interchangeably. (1.2)

2 DOSAGE AND ADMINISTRATION

- In adults: 720 mg by mouth, twice daily (1,440 mg total daily dose) on an empty stomach, 1 hour before or 2 hours after food intake. (2.1)
- In children: 5 years of age and older (who are at least 6 months post kidney transplant), 400 mg/m^2 by mouth, twice daily (up to a maximum of 720 mg twice daily). (2.2)
- Do not crush, chew, or cut tablet prior to ingestion. (2.3)

3 DOSAGE FORMS AND STRENGTHS

Myfortic is available as 180 mg and 360 mg tablets. (3)

4 CONTRAINDICATIONS

History of hypersensitivity, including anaphylaxis, to mycophenolate sodium, mycophenolic acid (MPA), mycophenolate mofetil, or to any of its excipients. (4)

5 WARNINGS AND PRECAUTIONS

- New or Reactivated Viral Infections: Consider reducing immunosuppression. (5.5)
- Blood Dyscrasias, including Pure Red Cell Aplasia (PRCA): Monitor for neutropenia or anemia; consider treatment interruption or dose reduction. (5.6)
- Serious GI Tract Complications (gastrointestinal bleeding, perforations and ulcers): Administer with caution to patients with active digestive system disease. (5.7)
- Hypersensitivity Reactions: Discontinue Myfortic; treat and monitor until signs and symptoms resolve. (5.9)
- Immunizations: Avoid live attenuated vaccines. (5.10)
- Patients with Hereditary Deficiency of Hypoxanthine-guanine Phosphoribosyl-transferase (HGPRT): May cause exacerbation of disease symptoms; avoid use. (5.11)
- Blood Donation: Avoid during therapy and for 6 weeks thereafter. (5.12)
- Semen Donation: Avoid during therapy and for 90 days thereafter. (5.13)

6 ADVERSE REACTIONS

Most common adverse reactions (≥ 20%): anemia, leukopenia, constipation, nausea, diarrhea, vomiting, dyspepsia, urinary tract infection, CMV infection, insomnia, and postoperative pain. (6.2)

To report SUSPECTED ADVERSE REACTIONS, contact Novartis Pharmaceuticals Corporation at 1-888-669-6682 or FDA at 1-800-FDA-1088 or www.fda.gov/medwatch.

7 DRUG INTERACTIONS

- Antacids with Magnesium and Aluminum Hydroxides: Decreases concentrations of MPA; concomitant use is not recommended. (7.1)
- Azathioprine: Competition for purine metabolism; concomitant administration is not recommended. (7.2)
- Cholestyramine, Bile Acid Sequestrates, Oral Activated Charcoal, and Other Drugs that Interfere with Enterohepatic Recirculation: May decrease MPA concentrations; concomitant use is not recommended. (7.3)
- Sevelamer: May decrease MPA concentrations; concomitant use is not recommended. (7.4)
- Cyclosporine: May decrease MPA concentrations; exercise caution when switching from cyclosporine to other drugs or from other drugs to cyclosporine. (7.5)
- Norfloxacin and Metronidazole: May decrease MPA concentrations; concomitant use with both drugs is not recommended. (7.6)
- Rifampin: May decrease MPA concentrations; concomitant use is not recommended unless the benefit outweighs the risk. (7.7)
- Hormonal Contraceptives: May reduce the effectiveness of oral contraceptives. Additional barrier contraceptive methods must be used. (5.2, 7.8)
- Acyclovir, Valacyclovir, Ganciclovir, Valganciclovir, and Other Drugs that Undergo Renal Tubular Secretion: May increase concentrations of mycophenolic acid glucuronide (MPAG) and coadministered drug; monitor blood cell counts. (7.9)

8 USE IN SPECIFIC POPULATIONS

- Male Patients: Sexually active male patients and/or their female partners are recommended to use effective contraception during treatment of the male patient and for at least 90 days after cessation of treatment. (8.3)

FULL PRESCRIBING INFORMATION

WARNING: EMBRYO-FETAL TOXICITY, MALIGNANCIES, AND SERIOUS INFECTIONS

- Use during pregnancy is associated with increased risks of pregnancy loss and congenital malformations. Avoid if safer treatment options are available. Females of reproductive potential must be counseled regarding pregnancy prevention and planning [see Warnings and Precautions (5.1), Use in Specific Populations (8.1, 8.3)].
- Only physicians experienced in immunosuppressive therapy and management of organ transplant patients should prescribe Myfortic. Patients receiving Myfortic should be managed in facilities equipped and staffed with adequate laboratory and supportive medical resources. The physician responsible for maintenance therapy should have complete information requisite for the follow-up of the patient [see Warnings and Precautions (5.2)].
- Increased risk of development of lymphoma and other malignancies, particularly of the skin, due to immunosuppression [see Warnings and Precautions (5.3)].
- Increased susceptibility to bacterial, viral, fungal, and protozoal infections, including opportunistic infections [see Warnings and Precautions (5.4, 5.5)].

1 INDICATIONS AND USAGE

1.1 Prophylaxis of Organ Rejection in Kidney Transplant

Myfortic® (mycophenolic acid) is indicated for the prophylaxis of organ rejection in adult patients receiving a kidney transplant.

Myfortic is indicated for the prophylaxis of organ rejection in pediatric patients 5 years of age and older who are at least 6 months post kidney transplant.

Myfortic is to be used in combination with cyclosporine and corticosteroids.

1.2 Limitations of Use

Myfortic delayed-release tablets and mycophenolate mofetil (MMF) tablets and capsules should not be used interchangeably without physician supervision because the rate of absorption following the administration of these two products is not equivalent.

2 DOSAGE AND ADMINISTRATION

2.1 Dosage in Adult Kidney Transplant Patients

The recommended dose of Myfortic is 720 mg administered twice daily (1,440 mg total daily dose).

2.2 Dosage in Pediatric Kidney Transplant Patients

The recommended dose of Myfortic in conversion (at least 6 months post-transplant) pediatric patients age 5 years and older is 400 mg/m^2 body surface area (BSA) administered twice daily (up to a maximum dose of 720 mg administered twice daily).

2.3 Administration

Myfortic tablets should be taken on an empty stomach, 1 hour before or 2 hours after food intake [see Clinical Pharmacology (12.3)].

Myfortic tablets should not be crushed, chewed, or cut prior to ingesting. The tablets should be swallowed whole in order to maintain the integrity of the enteric coating.

Pediatric patients with a BSA of 1.19 m^2 to 1.58 m^2 may be dosed either with three Myfortic 180 mg tablets, or one 180 mg tablet plus one 360 mg tablet twice daily (1,080 mg daily dose). Patients with a BSA of > 1.58 m^2 may be dosed either with four Myfortic 180 mg tablets, or two Myfortic 360 mg tablets twice daily (1,440 mg daily dose). Pediatric doses for patients with BSA < 1.19 m^2 cannot be accurately administered using currently available formulations of Myfortic tablets.

3 DOSAGE FORMS AND STRENGTHS

Myfortic is available as 180 mg and 360 mg tablets.

Table 1: Description of Myfortic (mycophenolic acid) Delayed-Release Tablets
Dosage strength | 180 mg tablet | 360 mg tablet
Active ingredient | mycophenolic acid as mycophenolate sodium | mycophenolic acid as mycophenolate sodium
Appearance | Lime green film-coated round tablet with bevelled edges | Pale orange-red film-coated ovaloid tablet
Imprint | “C” on one side | “CT” on one side

4 CONTRAINDICATIONS

Myfortic is contraindicated in patients with a history of hypersensitivity, including anaphylaxis, to mycophenolate sodium, mycophenolic acid (MPA), mycophenolate mofetil, or to any of its excipients [see Warnings and Precautions (5.9), Adverse Reactions (6.2)].

5 WARNINGS AND PRECAUTIONS

5.1 Embryo-Fetal Toxicity

Use of Myfortic during pregnancy is associated with an increased risk of first trimester pregnancy loss and an increased risk of congenital malformations, especially external ear and other facial abnormalities, including cleft lip and palate, and anomalies of the distal limbs, heart, esophagus, kidney, and nervous system. Females of reproductive potential must be aware of these risks and must be counseled regarding pregnancy prevention and planning. Avoid use of Myfortic during pregnancy if safer treatment options are available [see Use in Specific Populations (8.1, 8.3)].

5.2 Management of Immunosuppression

Only physicians experienced in immunosuppressive therapy and management of organ transplant patients should prescribe Myfortic. Patients receiving the drug should be managed in facilities equipped and staffed with adequate laboratory and supportive medical resources. The physicians responsible for maintenance therapy should have complete information requisite for the follow-up of the patient [see Boxed Warning].

5.3 Lymphoma and Other Malignancies

Patients receiving immunosuppressants, including Myfortic, are at increased risk of developing lymphomas and other malignancies, particularly of the skin [see Adverse Reactions (6)]. The risk appears to be related to the intensity and duration of immunosuppression rather than to the use of any specific agent.

As usual for patients with increased risk for skin cancer, exposure to sunlight and UV light should be limited by wearing protective clothing and using a broad-spectrum sunscreen with a high protection factor.

Post-transplant lymphoproliferative disorder (PTLD) has been reported in immunosuppressed organ transplant recipients. The majority of PTLD events appear related to Epstein-Barr Virus (EBV) infection. The risk of PTLD appears greatest in those individuals who are EBV seronegative, a population which includes many young children.

5.4 Serious Infections

Patients receiving immunosuppressants, including Myfortic, are at increased risk of developing bacterial, viral, fungal, and protozoal infections, and new or reactivated viral infections, including opportunistic infections [see Warnings and Precautions (5.5)]. These infections may lead to serious, including fatal outcomes. Because of the danger of oversuppression of the immune system which can increase susceptibility to infection, combination immunosuppressant therapy should be used with caution.

5.5 New or Reactivated Viral Infections

Polyomavirus associated nephropathy (PVAN), JC virus-associated progressive multifocal leukoencephalopathy (PML), cytomegalovirus (CMV) infections, reactivation of hepatitis B (HBV) or hepatitis C (HCV), SARS-CoV-2 infection, have been reported in patients treated with immunosuppressants, including MPA derivatives Myfortic and MMF. Reduction in immunosuppression should be considered for patients who develop evidence of new or reactivated viral infections. Physicians should also consider the risk that reduced immunosuppression represents to the functioning allograft.

PVAN, especially due to BK virus infection, is associated with serious outcomes, including deteriorating renal function and renal graft loss. Patient monitoring may help detect patients at risk for PVAN.

PML, which is sometimes fatal, commonly presents with hemiparesis, apathy, confusion, cognitive deficiencies, and ataxia. Risk factors for PML include treatment with immunosuppressant therapies and impairment of immune function. In immunosuppressed patients, physicians should consider PML in the differential diagnosis in patients reporting neurological symptoms and consultation with a neurologist should be considered as clinically indicated.

The risk of CMV viremia and CMV disease is highest among transplant recipients seronegative for CMV at time of transplant who receive a graft from a CMV seropositive donor. Therapeutic approaches to limiting CMV disease exist and should be routinely provided. Patient monitoring may help detect patients at risk for CMV disease [see Adverse Reactions (6.1)].

Viral reactivation has been reported in patients infected with HBV or HCV. Monitoring infected patients for clinical and laboratory signs of active HBV or HCV infection is recommended.

5.6 Blood Dyscrasias, Including Pure Red Cell Aplasia

Cases of pure red cell aplasia (PRCA) have been reported in patients treated with MPA derivatives in combination with other immunosuppressive agents. The mechanism for MPA derivatives induced PRCA is unknown; the relative contribution of other immunosuppressants and their combinations in an immunosuppressive regimen is also unknown. In some cases, PRCA was found to be reversible with dose reduction or cessation of therapy with MPA derivatives. In transplant patients, however, reduced immunosuppression may place the graft at risk. Changes to Myfortic therapy should only be undertaken under appropriate supervision in transplant recipients in order to minimize the risk of graft rejection.

Patients receiving Myfortic should be monitored for blood dyscrasias (e.g., neutropenia or anemia). The development of neutropenia may be related to Myfortic itself, concomitant medications, viral infections, or some combination of these reactions. Complete blood count should be performed weekly during the first month, twice monthly for the second and the third month of treatment, then monthly through the first year. If blood dyscrasias occur [neutropenia develops (ANC < 1.3 × 10^3/mcL) or anemia], dosing with Myfortic should be interrupted or the dose reduced, appropriate tests performed, and the patient managed accordingly.

5.7 Serious GI Tract Complications

Gastrointestinal bleeding (requiring hospitalization), intestinal perforations, gastric ulcers, and duodenal ulcers have been reported in patients treated with Myfortic. Myfortic should be administered with caution in patients with active serious digestive system disease.

5.8 Acute Inflammatory Syndrome Associated With Mycophenolate Products

Acute inflammatory syndrome (AIS) has been reported with the use of mycophenolate products, and some cases have resulted in hospitalization. AIS is a paradoxical pro-inflammatory reaction characterized by fever, arthralgias, arthritis, muscle pain and elevated inflammatory markers, including, C-reactive protein and erythrocyte sedimentation rate, without evidence of infection or underlying disease recurrence. Symptoms occur within weeks to months of initiation of treatment or a dose increase. After discontinuation, improvement of symptoms and inflammatory markers are usually observed within 24 to 48 hours.

Monitor patients for symptoms and laboratory parameters of AIS when starting treatment with mycophenolate products or when increasing the dosage. Discontinue treatment and consider other treatment alternatives based on the risk and benefit for the patient.

5.9 Hypersensitivity Reactions

Postmarketing cases of hypersensitivity reactions, including angioedema and anaphylaxis, have been reported with Myfortic. These reactions generally occurred within hours to the next day after initiating Myfortic. If signs or symptoms of a hypersensitivity reaction occur, discontinue Myfortic; treat and monitor until signs and symptoms resolve [see Contraindications (4)].

5.10 Immunizations

During treatment with Myfortic, the use of live attenuated vaccines should be avoided and patients should be advised that vaccinations may be less effective. Advise patients to discuss with the physician before seeking any immunizations.

5.11 Rare Hereditary Deficiencies

Myfortic is an inosine monophosphate dehydrogenase inhibitor (IMPDH inhibitor). Myfortic should be avoided in patients with rare hereditary deficiency of hypoxanthine-guanine phosphoribosyl-transferase (HGPRT), such as Lesch-Nyhan and Kelley-Seegmiller syndromes because it may cause an exacerbation of disease symptoms characterized by the overproduction and accumulation of uric acid leading to symptoms associated with gout, such as acute arthritis, tophi, nephrolithiasis or urolithiasis, and renal disease, including renal failure.

5.12 Blood Donation

Patients should not donate blood during therapy and for at least 6 weeks following discontinuation of Myfortic because their blood or blood products might be administered to a female of reproductive potential or a pregnant woman.

5.13 Semen Donation

Based on animal data, men should not donate semen during therapy and for 90 days following discontinuation of Myfortic [see Use in Specific Populations (8.3)].

6 ADVERSE REACTIONS

The following adverse reactions are discussed in greater detail in other sections of the label.

- Embryo-Fetal Toxicity [see Boxed Warning, Warnings and Precautions (5.1)]
- Lymphomas and Other Malignancies [see Boxed Warning, Warnings and Precautions (5.3)]
- Serious Infections [see Boxed Warning, Warnings and Precautions (5.4)]
- New or Reactivated Viral Infections [see Warnings and Precautions (5.5)]
- Blood Dyscrasias, Including Pure Red Cell Aplasia [see Warnings and Precautions (5.6)]
- Serious GI Tract Complications [see Warnings and Precautions (5.7)]
- Acute Inflammatory Syndrome Associated with Mycophenolate Products [see Warnings and Precautions (5.8)]
- Hypersensitivity Reactions [see Warnings and Precautions (5.9)]
- Rare Hereditary Deficiencies [see Warnings and Precautions (5.11)]

6.1 Clinical Studies Experience

Because clinical trials are conducted under widely varying conditions, adverse reaction rates observed in the clinical trials of a drug cannot be directly compared to rates in the clinical trials of another drug and may not reflect the rates observed in practice.

The data described below derive from two randomized, comparative, active-controlled, double-blind, double-dummy trials in prevention of acute rejection in de novo and converted stable kidney transplant patients.

In the de novo trial, patients were administered either Myfortic 1.44 grams per day (N = 213) or MMF 2 grams per day (N = 210) within 48 hours post-transplant for 12 months in combination with cyclosporine, USP MODIFIED and corticosteroids. Forty-one percent of patients also received antibody therapy as induction treatment. In the conversion trial, renal transplant patients who were at least 6 months post-transplant and receiving 2 grams per day MMF in combination with cyclosporine USP MODIFIED, with or without corticosteroids for at least two weeks prior to entry in the trial were randomized to Myfortic 1.44 grams per day (N = 159) or MMF 2 grams per day (N = 163) for 12 months.

The average age of patients in both studies was 47 years and 48 years (de novo study and conversion study, respectively), ranging from 22 to 75 years. Approximately 66% of patients were male; 82% were white, 12% were black, and 6% other races. About 40% of patients were from the United States and 60% from other countries.

In the de novo trial, the overall incidence of discontinuation due to adverse reactions was 18% (39/213) and 17% (35/210) in the Myfortic and MMF arms, respectively. The most common adverse reactions leading to discontinuation in the Myfortic arm were graft loss (2%), diarrhea (2%), vomiting (1%), renal impairment (1%), CMV infection (1%), and leukopenia (1%). The overall incidence of patients reporting dose reduction at least once during the 0- to 12-month study period was 59% and 60% in the Myfortic and MMF arms, respectively. The most frequent reasons for dose reduction in the Myfortic arm were adverse reactions (44%), dose reductions according to protocol guidelines (17%), dosing errors (11%) and missing data (2%).

The most common adverse reactions (≥ 20%) associated with the administration of Myfortic were anemia, leukopenia, constipation, nausea, diarrhea, vomiting, dyspepsia, urinary tract infection, CMV infection, insomnia, and postoperative pain.

The adverse reactions reported in ≥ 10% of patients in the de novo trial are presented in Table 2 below.

Table 2: Adverse Reactions (%) Reported in ≥ 10% of De novo Kidney Transplant Patients in Either Treatment Group
 | De novo Renal Trial**
System organ class adverse drug reactions | Myfortic 1.44 grams per day (n = 213) (%) | Mycophenolate mofetil (MMF) 2 grams per day (n = 210) (%)
Blood and lymphatic system disorders
Anemia | 22 | 22
Leukopenia | 19 | 21
Gastrointestinal system disorders
Constipation | 38 | 40
Nausea | 29 | 27
Diarrhea | 24 | 25
Vomiting | 23 | 20
Dyspepsia | 23 | 19
Abdominal pain upper | 14 | 14
Flatulence | 10 | 13
General and administrative site disorders
Edema | 17 | 18
Edema lower limb | 16 | 17
Pyrexia | 13 | 19
Investigations
Increased blood creatinine | 15 | 10
Infections and infestations
Urinary tract infection | 29 | 33
CMV infection | 20 | 18
Metabolism and nutrition disorders
Hypocalcemia | 11 | 15
Hyperuricemia | 13 | 13
Hyperlipidemia | 12 | 10
Hypokalemia | 13 | 9
Hypophosphatemia | 11 | 9
Musculoskeletal, connective tissue and bone disorders
Back pain | 12 | 6
Arthralgia | 7 | 11
Nervous system disorder
Insomnia | 24 | 24
Tremor | 12 | 14
Headache | 13 | 11
Vascular disorders
Hypertension | 18 | 18
**The trial was not designed to support comparative claims for Myfortic for the adverse reactions reported in this table.

Table 3 summarizes the incidence of opportunistic infections in de novo transplant patients.

Table 3: Viral and Fungal Infections (%) Reported Over 0 to 12 Months
 | De novo Renal Trial
 | Myfortic 1.44 grams per day (n = 213) (%) | Mycophenolate mofetil (MMF) 2 grams per day (n = 210) (%)
Any cytomegalovirus | 22 | 21
- Cytomegalovirus disease | 5 | 4
Herpes simplex | 8 | 6
Herpes zoster | 5 | 4
Any fungal infection | 11 | 12
- Candida NOS | 6 | 6
- Candida albicans | 2 | 4

Lymphoma developed in 2 de novo patients (1%), (1 diagnosed 9 days after treatment initiation) and in 2 conversion patients (1%) receiving Myfortic with other immunosuppressive agents in the 12-month controlled clinical trials.

Nonmelanoma skin carcinoma occurred in 1% de novo and 12% conversion patients. Other types of malignancy occurred in 1% de novo and 1% conversion patients [see Warnings and Precautions (5.3)].

The adverse reactions reported in less than 10% of de novo or conversion patients treated with Myfortic in combination with cyclosporine and corticosteroids are listed in Table 4.

Table 4: Adverse Reactions Reported in < 10% of Patients Treated With Myfortic in Combination With Cyclosporine* and Corticosteroids
Blood and lymphatic disorders | Lymphocele, thrombocytopenia
Cardiac disorder | Tachycardia
Eye disorder | Vision blurred
Gastrointestinal disorders | Abdominal pain, abdominal distension, gastroesophageal reflux disease, gingival hyperplasia
General disorders and administration-site conditions | Fatigue, peripheral edema
Infections and infestations | Nasopharyngitis, herpes simplex, upper respiratory infection, oral candidiasis, herpes zoster, sinusitis, influenza, wound infection, implant infection, pneumonia, sepsis
Investigations | Hemoglobin decrease, liver function tests abnormal
Metabolism and nutrition disorders | Hypercholesterolemia, hyperkalemia, hypomagnesemia, diabetes mellitus, hyperglycemia
Musculoskeletal and connective tissue disorders | Arthralgia, pain in limb, peripheral swelling, muscle cramps, myalgia
Nervous system disorders | Dizziness (excluding vertigo)
Psychiatric disorders | Anxiety
Renal and urinary disorders | Renal tubular necrosis, renal impairment, hematuria, urinary retention
Respiratory, thoracic and mediastinal disorders | Cough, dyspnea, dyspnea exertional
Skin and subcutaneous tissue disorders | Acne, pruritus, rash
Vascular disorders | Hypertension aggravated, hypotension
*USP MODIFIED.

The following additional adverse reactions have been associated with the exposure to MPA when administered as a sodium salt or as mofetil ester:

Gastrointestinal: Intestinal perforation, gastrointestinal hemorrhage, gastric ulcers, duodenal ulcers [see Warnings and Precautions (5.7)], colitis (including CMV colitis), pancreatitis, esophagitis, and ileus.

Infections: Serious life-threatening infections, such as meningitis and infectious endocarditis, tuberculosis, and atypical mycobacterial infection [see Warnings and Precautions (5.4)].

Respiratory: Interstitial lung disorders, including fatal pulmonary fibrosis.

6.2 Postmarketing Experience

The following adverse reactions have been identified during post-approval use of Myfortic or other MPA derivatives. Because these reactions are reported voluntarily from a population of uncertain size, it is not always possible to reliably estimate their frequency or establish a causal relationship to drug exposure:

- Congenital malformations, including ear, facial, cardiac and nervous system malformations and an increased incidence of first trimester pregnancy loss have been reported following exposure to MMF during pregnancy [see Boxed Warning, Warnings and Precautions (5.1)].
- Infections [see Warnings and Precautions (5.4, 5.5)]
  - Cases of progressive multifocal leukoencephalopathy (PML), sometimes fatal.
  - Polyomavirus associated nephropathy (PVAN), especially due to BK virus infection, associated with serious outcomes, including deteriorating renal function and renal graft loss.
  - Viral reactivation in patients infected with HBV or HCV.
- Cases of pure red cell aplasia (PRCA) have been reported in patients treated with MPA derivatives in combination with other immunosuppressive agents [see Warnings and Precautions (5.6)].
- Hypersensitivity reactions, including anaphylaxis and angioedema [see Warnings and Precautions (5.9)].

The following additional adverse reactions have been identified during post-approval use of Myfortic: agranulocytosis, asthenia, osteomyelitis, lymphadenopathy, lymphopenia, wheezing, dry mouth, gastritis, peritonitis, anorexia, alopecia, pulmonary edema, Kaposi’s sarcoma, de novo purine synthesis inhibitors-associated acute inflammatory syndrome.

7 DRUG INTERACTIONS

7.1 Antacids With Magnesium and Aluminum Hydroxides

Concomitant use of Myfortic and antacids decreased plasma concentrations of mycophenolic acid (MPA). It is recommended that Myfortic and antacids not be administered simultaneously [see Clinical Pharmacology (12.3)].

7.2 Azathioprine

Given that azathioprine and MMF inhibit purine metabolism, it is recommended that Myfortic not be administered concomitantly with azathioprine or MMF.

7.3 Cholestyramine, Bile Acid Sequestrates, Oral Activated Charcoal and Other Drugs That Interfere With Enterohepatic Recirculation

Drugs that interrupt enterohepatic recirculation may decrease MPA plasma concentrations when coadministered with MMF. Therefore, do not administer Myfortic with cholestyramine or other agents that may interfere with enterohepatic recirculation or drugs that may bind bile acids, e.g., bile acid sequestrates or oral activated charcoal, because of the potential to reduce the efficacy of Myfortic [see Clinical Pharmacology (12.3)].

7.4 Sevelamer

Concomitant administration of sevelamer and MMF may decrease MPA plasma concentrations. Sevelamer and other calcium-free phosphate binders should not be administered simultaneously with Myfortic [see Clinical Pharmacology (12.3)].

7.5 Cyclosporine

Cyclosporine inhibits the enterohepatic recirculation of MPA, and therefore, MPA plasma concentrations may be decreased when Myfortic is coadministered with cyclosporine. Clinicians should be aware that there is also a potential change of MPA plasma concentrations after switching from cyclosporine to other immunosuppressive drugs or from other immunosuppressive drugs to cyclosporine in patients concomitantly receiving Myfortic [see Clinical Pharmacology (12.3)].

7.6 Norfloxacin and Metronidazole

MPA plasma concentrations may be decreased when MMF is administrated with norfloxacin and metronidazole. Therefore, Myfortic is not recommended to be given with the combination of norfloxacin and metronidazole. Although there will be no effect on MPA plasma concentrations when Myfortic is concomitantly administered with norfloxacin or metronidazole when given separately [see Clinical Pharmacology (12.3)].

7.7 Rifampin

The concomitant administration of MMF and rifampin may decrease MPA plasma concentrations. Therefore, Myfortic is not recommended to be given with rifampin concomitantly unless the benefit outweighs the risk [see Clinical Pharmacology (12.3)].

7.8 Hormonal Contraceptives

In a drug interaction study, mean levonorgestrel AUC was decreased by 15% when coadministered with MMF. Although Myfortic may not have any influence on the ovulation-suppressing action of oral contraceptives, additional barrier contraceptive methods must be used when Myfortic is coadministered with hormonal contraceptives (e.g., birth control pill, transdermal patch, vaginal ring, injection, and implant) [see Warnings and Precautions (5.1), Use in Specific Populations (8.3), Clinical Pharmacology (12.3)].

7.9 Acyclovir (Valacyclovir), Ganciclovir (Valganciclovir), and Other Drugs That Undergo Renal Tubular Secretion

The coadministration of MMF and acyclovir or ganciclovir may increase plasma concentrations of mycophenolic acid glucuronide (MPAG) and acyclovir/valacyclovir/ganciclovir/valganciclovir as their coexistence competes for tubular secretion. Both acyclovir/valacyclovir/ganciclovir/valganciclovir and MPAG concentrations will be also increased in the presence of renal impairment.

Acyclovir/valacyclovir/ganciclovir/valganciclovir may be taken with Myfortic; however, during the period of treatment, physicians should monitor blood cell counts [see Clinical Pharmacology (12.3)].

7.10 Ciprofloxacin, Amoxicillin Plus Clavulanic Acid and Other Drugs That Alter the Gastrointestinal Flora

Drugs that alter the gastrointestinal flora, such as ciprofloxacin or amoxicillin plus clavulanic acid may interact with MMF by disrupting enterohepatic recirculation. Interference of MPAG hydrolysis may lead to less MPA available for absorption when Myfortic is concomitantly administered with ciprofloxacin or amoxicillin plus clavulanic acid. The clinical relevance of this interaction is unclear; however, no dose adjustment of Myfortic is needed when coadministered with these drugs [see Clinical Pharmacology (12.3)].

7.11 Pantoprazole

Administration of pantoprazole at a dose of 40 mg twice daily for 4 days to healthy volunteers did not alter the pharmacokinetics of a single dose of Myfortic [see Clinical Pharmacology (12.3)].

8 USE IN SPECIFIC POPULATIONS

8.1 Pregnancy

Pregnancy Exposure Registry

There is a pregnancy exposure registry that monitors pregnancy outcomes in women exposed to mycophenolate during pregnancy and those becoming pregnant within 6 weeks of discontinuing Myfortic treatment. To report a pregnancy or obtain information about the registry, visit www.mycophenolateREMS.com or call 1-800-617-8191.

Risk Summary

Following oral or intravenous (IV) administration, MMF is metabolized to mycophenolic acid (MPA), the active ingredient in Myfortic and the active form of the drug. Use of MMF during pregnancy is associated with an increased risk of first trimester pregnancy loss and an increased risk of multiple congenital malformations in multiple organ systems (see Human Data). Oral administration of mycophenolate to rats and rabbits during the period of organogenesis produced congenital malformations and pregnancy loss at doses less than the recommended clinical dose (0.05 and 1.1 times exposure at the recommended clinical doses in kidney transplant patients for rats and rabbits, respectively) (see Animal Data).

Risks and benefits of Myfortic should be discussed with the patient. When appropriate, consider alternative immunosuppressants with less potential for embryo-fetal toxicity.

The estimated background risk of pregnancy loss and congenital malformations in organ transplant populations is not clear. In the U.S. general population, the estimated background risk of major birth defects and miscarriage in clinically recognized pregnancies is 2% to 4% and 15% to 20%, respectively.

Data

Human Data

A spectrum of congenital malformations (including multiple malformations in individual newborns) has been reported in 23% to 27% of live births in MMF exposed pregnancies, based on published data from pregnancy registries. Malformations that have been documented include external ear, eye, and other facial abnormalities, including cleft lip and palate, and anomalies of the distal limbs, heart, esophagus, kidney, and nervous system. Based on published data from pregnancy registries, the risk of first trimester pregnancy loss has been reported at 45% to 49% following MMF exposure.

Animal Data

In animal reproductive toxicology studies, congenital malformations and pregnancy loss occurred when pregnant rats and rabbits received mycophenolate at dose multiples equivalent to and less than the recommended human dose. Oral administration of mycophenolate sodium to pregnant rats from Gestational Day 7 to Day 16 at a dose as low as 1 mg per kg resulted in malformations including anophthalmia, exencephaly, and umbilical hernia. The systemic exposure at this dose represents 0.05 times the clinical exposure at the human dose of 1,440 mg per day of Myfortic. Oral administration of mycophenolate to pregnant rabbits from Gestational Day 7 to Day 19 resulted in embryofetal lethality and malformations, including ectopia cordis, ectopic kidneys, diaphragmatic hernia, and umbilical hernia at doses equal to or greater than 80 mg per kg per day, in the absence of maternal toxicity. This corresponds to about 1.1 times the recommended clinical dose based on BSA.

8.2 Lactation

Risk Summary

There are no data on the presence of mycophenolate in human milk, or the effects on milk production. There are limited data in the National Transplantation Pregnancy Registry on the effects of mycophenolate on a breastfed child (see Data). Studies in rats treated with MMF have shown mycophenolic acid to be present in milk. Because available data are limited, it is not possible to exclude potential risks to a breastfeeding infant.

The developmental and health benefits of breastfeeding should be considered along with the mother’s clinical need for Myfortic and any potential adverse effects on the breastfed infant from Myfortic or from the underlying maternal condition. Because available data are limited, it is not possible to exclude potential risks to a breastfeeding infant.

Data

Limited information is available from the National Transplantation Pregnancy Registry. Of seven infants reported by the National Transplantation Pregnancy Registry to have been breastfed while the mother was taking mycophenolate, all were born at 34 to 40 weeks gestation and breastfed for up to 14 months. No adverse events were reported.

8.3 Females and Males of Reproductive Potential

Females of reproductive potential must be made aware of the increased risk of first trimester pregnancy loss and congenital malformations and must be counseled regarding pregnancy prevention and planning.

Pregnancy Planning

For female patients taking Myfortic who are considering pregnancy, consider alternative immunosuppressants with less potential for embryo-fetal toxicity. Risks and benefits of Myfortic should be discussed with the patient.

Pregnancy Testing

To prevent unplanned exposure during pregnancy, females of reproductive potential should have a serum or urine pregnancy test with a sensitivity of at least 25 mIU/mL immediately before starting Myfortic. Another pregnancy test with the same sensitivity should be done 8 to 10 days later. Repeat pregnancy tests should be performed during routine follow-up visits. Results of all pregnancy tests should be discussed with the patient. In the event of a positive pregnancy test, consider alternative immunosuppressants with less potential for embryo-fetal toxicity whenever possible.

Contraception

Female Patients

Females of reproductive potential taking Myfortic must receive contraceptive counseling and use acceptable contraception (see Table 5 for Acceptable Contraception Methods). Patients must use acceptable birth control during entire Myfortic therapy, and for 6 weeks after stopping Myfortic, unless the patient chooses abstinence (she chooses to avoid heterosexual intercourse completely).

Patients should be aware that Myfortic reduces blood levels of the hormones in the oral contraceptive pill and could theoretically reduce its effectiveness [see Patient Counseling Information (17), Drug Interactions (7.8)].

Table 5: Acceptable Contraception Methods for Females of Reproductive Potential
Pick from the following birth control options:
Option 1
Methods to use alone | Intrauterine devices (IUDs) Tubal sterilization Patient’s partner had a vasectomy

OR

Option 2 | Hormone methods choose 1 |  | Barrier methods choose 1
Choose one hormone method AND one barrier method | Estrogen and progesterone Oral Contraceptive Pill Transdermal patch Vaginal ring Progesterone-only Injection Implant | AND | Diaphragm with spermicide Cervical cap with spermicide Contraceptive sponge Male condom Female condom

OR

Option 3 | Barrier methods choose 1 |  | Barrier methods choose 1
Choose one barrier method from each column (must choose two methods) | Diaphragm with spermicide Cervical cap with spermicide Contraceptive sponge | AND | Male condom Female condom

Male Patients

Genotoxic effects have been observed in animal studies at exposures exceeding the human therapeutic exposures by approximately 2.5 times. Thus, the risk of genotoxic effects on sperm cells cannot be excluded. Based on this potential risk, sexually active male patients and/or their female partners are recommended to use effective contraception during treatment of the male patient and for at least 90 days after cessation of treatment. Also, based on the potential risk of genotoxic effects, male patients should not donate sperm during treatment with Myfortic and for at least 90 days after cessation of treatment [see Use in Specific Populations (8.1), Nonclinical Toxicology (13.1), Patient Counseling Information (17)].

8.4 Pediatric Use

The safety and effectiveness of Myfortic have been established in pediatric kidney transplant patients 5 to 16 years of age who were initiated on Myfortic at least 6 months post-transplant. Use of Myfortic in this age group is supported by evidence from adequate and well-controlled studies of Myfortic in a similar population of adult kidney transplant patients with additional pharmacokinetic data in pediatric kidney transplant patients [see Dosage and Administration (2.2, 2.3), Clinical Pharmacology (12.3)]. Pediatric doses for patients with BSA < 1.19 m^2 cannot be accurately administered using currently available formulations of Myfortic tablets.

The safety and effectiveness of Myfortic in de novo pediatric kidney transplant patients and in pediatric kidney transplant patients below the age of 5 years have not been established.

8.5 Geriatric Use

Clinical studies of Myfortic did not include sufficient numbers of subjects aged 65 and over to determine whether they respond differently from younger subjects. Of the 372 patients treated with Myfortic in the clinical trials, 6% (N = 21) were 65 years of age and older and 0.3% (N = 1) were 75 years of age and older. Other reported clinical experience has not identified differences in responses between the elderly and younger patients. In general, dose selection for an elderly patient should be cautious, reflecting the greater frequency of decreased hepatic, renal, or cardiac function, and of concomitant disease or other drug therapy.

10 OVERDOSAGE

Signs and Symptoms

There have been anecdotal reports of deliberate or accidental overdoses with Myfortic, whereas not all patients experienced related adverse reactions.

In those overdose cases in which adverse reactions were reported, the reactions fall within the known safety profile of the class. Accordingly, an overdose of Myfortic could possibly result in oversuppression of the immune system and may increase the susceptibility to infection, including opportunistic infections, fatal infections and sepsis. If blood dyscrasias occur (e.g., neutropenia with absolute neutrophil count < 1.5 x 10^3/mcL or anemia), it may be appropriate to interrupt or discontinue Myfortic.

Possible signs and symptoms of acute overdose could include the following: hematological abnormalities, such as leukopenia and neutropenia, and gastrointestinal symptoms, such as abdominal pain, diarrhea, nausea and vomiting, and dyspepsia.

Treatment and Management

General supportive measures and symptomatic treatment should be followed in all cases of overdosage. Although dialysis may be used to remove the inactive metabolite mycophenolic acid glucuronide (MPAG), it would not be expected to remove clinically significant amounts of the active moiety, mycophenolic acid, due to the 98% plasma protein binding of mycophenolic acid. By interfering with enterohepatic circulation of mycophenolic acid, activated charcoal or bile sequestrates, such as cholestyramine, may reduce the systemic mycophenolic acid exposure.

11 DESCRIPTION

Myfortic® (mycophenolic acid) delayed-release tablets are an enteric formulation of mycophenolate sodium that delivers the active moiety mycophenolic acid (MPA). Myfortic is an immunosuppressive agent. As the sodium salt, MPA is chemically designated as (E)-6-(4-hydroxy-6-methoxy-7-methyl-3-oxo-1,3-dihydroisobenzofuran-5-yl)-4-methylhex-4-enoic acid sodium salt.

Its empirical formula is C17H19O6Na. The molecular weight is 342.32 g/mol and the structural formula is:

Myfortic, as the sodium salt, is a white to off-white, crystalline powder and is highly soluble in aqueous media at physiological pH and practically insoluble in 0.1N hydrochloric acid.

Myfortic is available for oral use as delayed-release tablets containing either 180 mg or 360 mg of mycophenolic acid. Inactive ingredients include colloidal silicon dioxide, crospovidone, lactose anhydrous, magnesium stearate, povidone (K-30), and starch. The enteric coating of the tablet consists of hypromellose phthalate, titanium dioxide, iron oxide yellow, and indigotine (180 mg) or iron oxide red (360 mg).

12 CLINICAL PHARMACOLOGY

12.1 Mechanism of Action

Mycophenolic acid (MPA), an immunosuppressant, is an uncompetitive and reversible inhibitor of inosine monophosphate dehydrogenase (IMPDH), and therefore inhibits the de novo pathway of guanosine nucleotide synthesis without incorporation to DNA. T- and B-lymphocytes are critically dependent for their proliferation on de novo synthesis of purines, whereas other cell types can utilize salvage pathways. MPA has cytostatic effects on lymphocytes.

Mycophenolate sodium has been shown to prevent the occurrence of acute rejection in rat models of kidney and heart allotransplantation. Mycophenolate sodium also decreases antibody production in mice.

12.3 Pharmacokinetics

Myfortic exhibits linear and dose-proportional pharmacokinetics over the dose-range (360 mg to 2,160 mg) evaluated. The absolute bioavailability of Myfortic in stable renal transplant patients on cyclosporine was 72%. MPA is highly protein bound (> 98% bound to albumin). The predominant metabolite of MPA is the phenolic glucuronide (MPAG) which is pharmacologically inactive. A minor metabolite AcMPAG which is an acyl glucuronide of MPAG is also formed and has pharmacological activity comparable to MPA. MPAG undergoes renal elimination. A fraction of MPAG also undergoes biliary excretion, followed by deconjugation by gut flora and subsequent reabsorption as MPA. The mean elimination half-lives of MPA and MPAG ranged between 8 and 16 hours, and 13 and 17 hours, respectively.

Absorption

In vitro studies demonstrated that the enteric-coated Myfortic tablet does not release MPA under acidic conditions (pH < 5) as in the stomach but is highly soluble in neutral pH conditions as in the intestine. Following Myfortic oral administration without food in several pharmacokinetic studies conducted in renal transplant patients, consistent with its enteric-coated formulation, the median delay (Tlag) in the rise of MPA concentration ranged between 0.25 and 1.25 hours and the median time to maximum concentration (Tmax) of MPA ranged between 1.5 and 2.75 hours. In comparison, following the administration of MMF, the median Tmax ranged between 0.5 and 1.0 hours. In stable renal transplant patients on cyclosporine, USP MODIFIED based immunosuppression, gastrointestinal absorption and absolute bioavailability of MPA following the administration of Myfortic delayed-release tablet was 93% and 72%, respectively. Myfortic pharmacokinetics is dose proportional over the dose range of 360 mg to 2,160 mg.

Distribution

The mean (± SD) volume of distribution at steady state and elimination phase for MPA is 54 (± 25) L and 112 (± 48) L, respectively. MPA is highly protein bound to albumin, > 98%. The protein binding of MPAG is 82%. The free MPA concentration may increase under conditions of decreased protein binding (uremia, hepatic failure, and hypoalbuminemia).

Metabolism

MPA is metabolized principally by glucuronyl transferase to glucuronidated metabolites. The phenolic glucuronide of MPA, MPAG, is the predominant metabolite of MPA and does not manifest pharmacological activity. The acyl glucuronide is a minor metabolite and has comparable pharmacological activity to MPA. In stable renal transplant patients on cyclosporine, USP MODIFIED based immunosuppression, approximately 28% of the oral Myfortic dose was converted to MPAG by presystemic metabolism. The AUC ratio of MPA:MPAG:acyl glucuronide is approximately 1:24:0.28 at steady state. The mean clearance of MPA was 140 (± 30) mL/min.

Elimination

The majority of MPA dose administered is eliminated in the urine primarily as MPAG (> 60%) and approximately 3% as unchanged MPA following Myfortic administration to stable renal transplant patients. The mean renal clearance of MPAG was 15.5 (± 5.9) mL/min. MPAG is also secreted in the bile and available for deconjugation by gut flora. MPA resulting from the deconjugation may then be reabsorbed and produce a second peak of MPA approximately 6 to 8 hours after Myfortic dosing. The mean elimination half-life of MPA and MPAG ranged between 8 and 16 hours, and 13 and 17 hours, respectively.

Food Effect

Compared to the fasting state, administration of Myfortic 720 mg with a high-fat meal (55 g fat, 1000 calories) had no effect on the systemic exposure (AUC) of MPA. However, there was a 33% decrease in the maximal concentration (Cmax), a 3.5-hour delay in the Tlag (range, -6 to 18 hours), and 5.0-hour delay in the Tmax (range, -9 to 20 hours) of MPA. To avoid the variability in MPA absorption between doses, Myfortic should be taken on an empty stomach [see Dosage and Administration (2.3)].

Pharmacokinetics in Renal Transplant Patients

The mean pharmacokinetic parameters for MPA following the administration of Myfortic in renal transplant patients on cyclosporine, USP MODIFIED based immunosuppression are shown in Table 6. Single-dose Myfortic pharmacokinetics predicts multiple-dose pharmacokinetics. However, in the early post-transplant period, mean MPA AUC and Cmax were approximately one-half of those measured 6 months post-transplant.

After near equimolar dosing of Myfortic 720 mg twice daily and MMF 1,000 mg twice daily (739 mg as MPA) in both the single- and multiple-dose crossover trials, mean systemic MPA exposure (AUC) was similar.

Table 6: Mean ± SD Pharmacokinetic Parameters for MPA Following the Oral Administration of Myfortic to Renal Transplant Patients on Cyclosporine, USP MODIFIED Based Immunosuppression
Patient | Myfortic dosing | N | Dose (mg) | Tmaxa(h) | Cmax (mcg/mL) | AUC(0-12h) (mcg*h/mL)
Adult | Single | 24 | 720 | 2 (0.8-8) | 26.1 ± 12.0 | 66.5 ± 22.6b
Pediatricc | Single | 10 | 450/m^2 | 2.5 (1.5-24) | 36.3 ± 20.9 | 74.3 ± 22.5b
Adult | Multiple x6 days, twice daily | 10 | 720 | 2 (1.5-3.0) | 37.0 ± 13.3 | 67.9 ± 20.3
Adult | Multiple x28 days, twice daily | 36 | 720 | 2.5 (1.5-8) | 31.2 ± 18.1 | 71.2 ± 26.3
Adult | Chronic, multiple-dose, twice daily
 | 2 weeks post-transplant | 12 | 720 | 1.8 (1.0-5.3) | 15.0 ± 10.7 | 28.6 ± 11.5
 | 3 months post-transplant | 12 | 720 | 2 (0.5-2.5) | 26.2 ± 12.7 | 52.3 ± 17.4
 | 6 months post-transplant | 12 | 720 | 2 (0-3) | 24.1 ± 9.6 | 57.2 ± 15.3
Adult | Chronic, multiple-dose, twice daily | 18 | 720 | 1.5 (0-6) | 18.9 ± 7.9 | 57.4 ± 15.0
amedian (range).
bAUCinf..
cage range of 5 to 16 years.

Specific Populations

Patients with Renal Insufficiency: No specific pharmacokinetic studies in individuals with renal impairment were conducted with Myfortic. However, based on studies of renal impairment with MMF, MPA exposure is not expected to be appreciably increased over the range of normal to severely impaired renal function following Myfortic administration. In contrast, MPAG exposure would be increased markedly with decreased renal function; MPAG exposure being approximately 8-fold higher in the setting of anuria. Although dialysis may be used to remove the inactive metabolite MPAG, it would not be expected to remove clinically significant amounts of the active moiety MPA. This is in large part due to the high plasma protein binding of MPA.

Patients with Hepatic Insufficiency: No specific pharmacokinetic studies in individuals with hepatic impairment were conducted with Myfortic. In a single dose (MMF 1,000 mg) trial of 18 volunteers with alcoholic cirrhosis and 6 healthy volunteers, hepatic MPA glucuronidation processes appeared to be relatively unaffected by hepatic parenchymal disease when the pharmacokinetic parameters of healthy volunteers and alcoholic cirrhosis patients within this trial were compared. However, it should be noted that for unexplained reasons, the healthy volunteers in this trial had about a 50% lower AUC compared to healthy volunteers in other studies, thus making comparison between volunteers with alcoholic cirrhosis and healthy volunteers difficult. Effects of hepatic disease on this process probably depend on the particular disease. Hepatic disease, such as primary biliary cirrhosis, with other etiologies may show a different effect.

Pediatric Patients: Limited data are available on the use of Myfortic at a dose of 450 mg/m^2 body surface area in children. The mean MPA pharmacokinetic parameters for stable pediatric renal transplant patients, 5 to 16 years, on cyclosporine, USP MODIFIED are shown in Table 6. At the same dose administered based on body surface area, the respective mean Cmax and AUC of MPA determined in children were higher by 33% and 18% than those determined for adults. The clinical impact of the increase in MPA exposure is not known [see Dosage and Administration (2.2, 2.3)].

Male and Female Patients: There are no significant gender differences in Myfortic pharmacokinetics.

Geriatric Patients: Pharmacokinetics in the elderly have not been formally studied.

Racial or Ethnic Groups: Following a single dose administration of 720 mg of Myfortic to 18 Japanese and 18 Caucasian healthy subjects, the exposure (AUCinf) for MPA and MPAG were 15% and 22% lower in Japanese subjects compared to Caucasians. The peak concentrations (Cmax) for MPAG were similar between the two populations, however, Japanese subjects had 9.6% higher Cmax for MPA. These results do not suggest any clinically relevant differences.

Drug Interactions

Antacids With Magnesium and Aluminum Hydroxides:

Absorption of a single dose of Myfortic was decreased when administered to 12 stable kidney transplant patients also taking magnesium-aluminum-containing antacids (30 mL): the mean Cmax and AUC(0-t) values for MPA were 25% and 37% lower, respectively, than when Myfortic was administered alone under fasting conditions [see Drug Interactions (7.1)].

Pantoprazole:

In a trial conducted in 12 healthy volunteers, the pharmacokinetics of MPA were observed to be similar when a single dose of 720 mg of Myfortic was administered alone and following concomitant administration of Myfortic and pantoprazole, which was administered at a dose of 40 mg twice daily for 4 days [see Drug Interactions (7.11)].

The following drug interaction studies were conducted following the administration of MMF:

Cholestyramine:

Following single-dose oral administration of 1.5 grams MMF to 12 healthy volunteers pretreated with 4 grams three times daily of cholestyramine for 4 days, MPA AUC decreased approximately 40%. This decrease is consistent with interruption of enterohepatic recirculation which may be due to binding of recirculating MPAG with cholestyramine in the intestine [see Drug Interactions (7.3)].

Sevelamer:

Concomitant administration of sevelamer and MMF in stable adult and pediatric kidney transplant patients decreased the mean MPA Cmax and AUC(0-12h) by 36% and 26%, respectively [see Drug Interactions (7.4)].

Cyclosporine:

Cyclosporine (Sandimmune®) pharmacokinetics (at doses of 275 to 415 mg/day) were unaffected by single and multiple doses of 1.5 grams twice daily of MMF in 10 stable kidney transplant patients. The mean (± SD) AUC(0-12h) and Cmax of cyclosporine after 14 days of multiple doses of MMF were 3290 (± 822) ng•h/mL and 753 (± 161) ng/mL, respectively, compared to 3245 (± 1088) ng•h/mL and 700 (± 246) ng/mL, respectively, 1 week before administration of MMF.

A total of 73 de novo kidney allograft recipients on MMF therapy received either low dose cyclosporine withdrawal by 6 months post-transplant (50 to 100 ng/mL for up to 3 months post-transplant followed by complete withdrawal at month 6 post-transplant) or standard dose cyclosporine (150 to 300 ng/mL from baseline through month 4 post-transplant and 100 to 200 ng/mL thereafter). At month 12 post-transplant, the mean MPA (AUC(0-12h)) in the cyclosporine withdrawal group was approximately 40% higher, than that of the standard dose cyclosporine group.

Cyclosporine inhibits multidrug-resistance-associated protein 2 (MRP-2) transporter in the biliary tract, thereby preventing the excretion of MPAG into the bile that would lead to enterohepatic recirculation of MPA [see Drug Interactions (7.5)].

Norfloxacin and Metronidazole:

Following single-dose administration of MMF (1 g) to 11 healthy volunteers on Day 4 of a 5-day course of a combination of norfloxacin and metronidazole, the mean MPA AUC(0-48h) was reduced by 33% compared to the administration of MMF alone (p < 0.05). There was no significant effect on mean MPA AUC(0-48h) when MMF was concomitantly administered with norfloxacin or metronidazole separately. The mean (± SD) MPA AUC(0-48h) after coadministration of MMF with norfloxacin or metronidazole separately was 48.3 (± 24) mcg•h/mL and 42.7 (± 23) mcg•h/mL, respectively, compared with 56.2 (± 24) mcg•h/mL after administration of MMF alone [see Drug Interactions (7.6)].

Rifampin:

In a single heart-lung transplant patient on MMF therapy (1 gram twice daily), a 67% decrease in MPA exposure (AUC(0-12h)) was observed with concomitant administration of MMF and 600 mg rifampin daily.

In 8 kidney transplant patients on stable MMF therapy (1 gram twice daily), administration of 300 mg rifampin twice daily resulted in a 17.5% decrease in MPA AUC(0-12h) due to inhibition of enterohepatic recirculation of MPAG by rifampin. Rifampin coadministration also resulted in a 22.4% increase in MPAG AUC(0-12h) [see Drug Interactions (7.7)].

Oral Contraceptives:

In a drug-drug interaction trial, mean AUCs were similar for ethinyl estradiol and norethindrone, when coadministered with MMF as compared to administration of the oral contraceptives alone [see Drug Interactions (7.8)].

Acyclovir:

Coadministration of MMF (1 gram) and acyclovir (800 mg) to 12 healthy volunteers resulted in no significant change in MPA AUC and Cmax. However, MPAG and acyclovir plasma mean AUC(0-24h) were increased 10% and 18%, respectively. Because MPAG plasma concentrations are increased in the presence of kidney impairment, as are acyclovir concentrations, the potential exists for mycophenolate and acyclovir or its prodrug (e.g., valacyclovir) to compete for tubular secretion, further increasing the concentrations of both drugs [see Drug Interactions (7.9)].

Ganciclovir:

Following single-dose administration to 12 stable kidney transplant patients, no pharmacokinetic interaction was observed between MMF (1.5 grams) and intravenous ganciclovir (5 mg per kg). Mean (± SD) ganciclovir AUC and Cmax (n = 10) were 54.3 (± 19.0) mcg•h/mL and 11.5 (± 1.8) mcg/mL, respectively, after coadministration of the two drugs, compared to 51.0 (± 17.0) mcg•h/mL and 10.6 (± 2.0) mcg/mL, respectively, after administration of intravenous ganciclovir alone. The mean (± SD) AUC and Cmax of MPA (n = 12) after coadministration were 80.9 (± 21.6) mcg•h/mL and 27.8 (± 13.9) mcg/mL, respectively, compared to values of 80.3 (± 16.4) mcg•h/mL and 30.9 (± 11.2) mcg/mL, respectively, after administration of MMF alone.

Because MPAG plasma concentrations are increased in the presence of renal impairment, as are ganciclovir concentrations, the two drugs will compete for tubular secretion and thus further increases in concentrations of both drugs may occur. In patients with renal impairment in which MMF and ganciclovir or its prodrug (e.g., valganciclovir) are co-administered, patients should be monitored carefully [see Drug Interactions (7.9)].

Ciprofloxacin and Amoxicillin Plus Clavulanic Acid:

A total of 64 MMF-treated kidney transplant recipients received either oral ciprofloxacin 500 mg twice daily or amoxicillin plus clavulanic acid 375 mg three times daily for 7 or at least 14 days. Approximately 50% reductions in median trough MPA concentrations (predose) from baseline (MMF alone) were observed in 3 days following commencement of oral ciprofloxacin or amoxicillin plus clavulanic acid. These reductions in trough MPA concentrations tended to diminish within 14 days of antibiotic therapy and ceased within 3 days after discontinuation of antibiotics. The postulated mechanism for this interaction is an antibiotic-induced reduction in glucuronidase-possessing enteric organisms leading to a decrease in enterohepatic recirculation of MPA. The change in trough level may not accurately represent changes in overall MPA exposure; therefore, clinical relevance of these observations is unclear [see Drug Interactions (7.10)].

13 NONCLINICAL TOXICOLOGY

13.1 Carcinogenesis, Mutagenesis, Impairment of Fertility

In a 104-week oral carcinogenicity study in rats, mycophenolate sodium was not tumorigenic at daily doses up to 9 mg per kg, the highest dose tested. This dose resulted in approximately 0.6 to 1.2 times the systemic exposure (based on plasma AUC) observed in renal transplant patients at the recommended dose of 1,440 mg per day. Similar results were observed in a parallel study in rats performed with MMF. In a 104-week oral carcinogenicity study in mice, MMF was not tumorigenic at a daily dose level as high as 180 mg per kg (which corresponds to 0.6 times the recommended mycophenolate sodium therapeutic dose, based on body surface area).

The genotoxic potential of mycophenolate sodium was determined in five assays. Mycophenolate sodium was genotoxic in the mouse lymphoma/thymidine kinase assay, the micronucleus test in V79 Chinese hamster cells, and the in vivo mouse micronucleus assay. Mycophenolate sodium was not genotoxic in the bacterial mutation assay (Salmonella typhimurium TA 1535, 97a, 98, 100, and 102) or the chromosomal aberration assay in human lymphocytes.

Mycophenolate mofetil generated similar genotoxic activity. The genotoxic activity of mycophenolic acid (MPA) is probably due to the depletion of the nucleotide pool required for DNA synthesis as a result of the pharmacodynamic mode of action of MPA (inhibition of nucleotide synthesis).

Mycophenolate sodium had no effect on male rat fertility at daily oral doses as high as 18 mg per kg and exhibited no testicular or spermatogenic effects at daily oral doses of 20 mg per kg for 13 weeks (approximately 2 times the systemic exposure of MPA at the recommended therapeutic dose). No effects on female fertility were seen up to a daily dose of 20 mg per kg (approximately 3 times the systemic exposure of MPA at the recommended therapeutic dose).

14 CLINICAL STUDIES

14.1 Prophylaxis of Organ Rejection in Patients Receiving Allogeneic Renal Transplants

The safety and efficacy of Myfortic in combination with cyclosporine, USP MODIFIED and corticosteroids for the prevention of organ rejection was assessed in two multicenter, randomized, double-blind, active-controlled trials in de novo and conversion renal transplant patients compared to MMF.

The de novo trial was conducted in 423 renal transplant patients (ages 18–75 years) in Austria, Canada, Germany, Hungary, Italy, Norway, Spain, UK, and USA. Eighty-four percent of randomized patients received kidneys from deceased donors. Patients were excluded if they had second or multiorgan (e.g., kidney and pancreas) transplants, or previous transplant with any other organs; kidneys from non-heart beating donors; panel reactive antibodies (PRA) of > 50% at last assessment prior to transplantation, and presence of severe diarrhea, active peptic ulcer disease, or uncontrolled diabetes mellitus. Patients were administered either Myfortic 1.44 grams per day or MMF 2 grams per day within 48 hours post-transplant for 12 months in combination with cyclosporine, USP MODIFIED and corticosteroids. Forty-one percent of patients received antibody therapy as induction treatment. Treatment failure was defined as the first occurrence of biopsy-proven acute rejection, graft loss, death or lost to follow-up at 6 months.

The incidence of treatment failure was similar in Myfortic and MMF-treated patients at 6 and 12 months (Table 7). The cumulative incidence of graft loss, death and lost to follow-up at 12 months is also shown in Table 7.

Table 7: Treatment Failure in De novo Renal Transplant Patients (Percentage of Patients) at 6 and 12 Months of Treatment When Administered in Combination With Cyclosporinea and Corticosteroids
 | Myfortic 1.44 grams per day (n = 213) | Mycophenolate mofetil (MMF) 2 grams per day (n = 210)
6 Months | n (%) | n (%)
Treatment failureb | 55 (25.8) | 55 (26.2)
Biopsy-proven acute rejection | 46 (21.6) | 48 (22.9)
Graft loss | 7 (3.3) | 9 (4.3)
Death | 1 (0.5) | 2 (1.0)
Lost to follow-upc | 3 (1.4) | 0
12 Months | n (%) | n (%)
Graft loss or death or lost to follow-upd | 20 (9.4) | 18 (8.6)
Treatment failuree | 61 (28.6) | 59 (28.1)
Biopsy-proven acute rejection | 48 (22.5) | 51 (24.3)
Graft loss | 9 (4.2) | 9 (4.3)
Death | 2 (0.9) | 5 (2.4)
Lost to follow-upc | 5 (2.3) | 0
aUSP MODIFIED.
b95% confidence interval of the difference in treatment failure at 6 months (Myfortic–MMF) is (-8.7%, 8.0%).
cLost to follow-up indicates patients who were lost to follow-up without prior biopsy-proven acute rejection, graft loss or death.
dLost to follow-up indicates patients who were lost to follow-up without prior graft loss or death (9 Myfortic patients and 4 MMF patients).
e95% confidence interval of the difference in treatment failure at 12 months (Myfortic–MMF) is (-8.0%, 9.1%).

The conversion trial was conducted in 322 renal transplant patients (ages 18–75 years), who were at least 6 months post-transplant and had undergone primary or secondary, deceased donor, living related, or unrelated donor kidney transplant, stable graft function (serum creatinine < 2.3 mg/mL), no change in immunosuppressive regimen due to graft malfunction, and no known clinically significant physical and/or laboratory changes for at least 2 months prior to enrollment. Patients were excluded if they had 3 or more kidney transplants, multiorgan transplants (e.g., kidney and pancreas), previous organ transplants, evidence of graft rejection or who had been treated for acute rejection within 2 months prior to screening, clinically significant infections requiring continued therapy, presence of severe diarrhea, active peptic ulcer disease, or uncontrolled diabetes mellitus.

Patients received 2 grams per day MMF in combination with cyclosporine USP MODIFIED, with or without corticosteroids for at least two weeks prior to entry in the trial. Patients were randomized to Myfortic 1.44 grams per day or MMF 2 grams per day for 12 months. The trial was conducted in Austria, Belgium, Canada, Germany, Italy, Spain, and USA. Treatment failure was defined as the first occurrence of biopsy-proven acute rejection, graft loss, death, or lost to follow-up at 6 and 12 months.

The incidences of treatment failure at 6 and 12 months were similar between Myfortic and MMF-treated patients (Table 8). The cumulative incidence of graft loss, death and lost to follow-up at 12 months is also shown in Table 8.

Table 8: Treatment Failure in Conversion Transplant Patients (Percentage of Patients) at 6 and 12 Months of Treatment When Administered in Combination With Cyclosporinea and With or Without Corticosteroids
 | Myfortic 1.44 grams per day (n = 159) | Mycophenolate mofetil (MMF) 2 grams per day (n = 163)
6 Months | n (%) | n (%)
Treatment failureb | 7 (4.4) | 11 (6.7)
Biopsy-proven acute rejection | 2 (1.3) | 2 (1.2)
Graft loss | 0 | 1 (0.6)
Death | 0 | 1 (0.6)
Lost to follow-upc | 5 (3.1) | 7 (4.3)
12 Months | n (%) | n (%)
Graft loss or death or lost to follow-upd | 10 (6.3) | 17 (10.4)
Treatment failuree | 12 (7.5) | 20 (12.3)
Biopsy-proven acute rejection | 2 (1.3) | 5 (3.1)
Graft loss | 0 | 1 (0.6)
Death | 2 (1.3) | 4 (2.5)
Lost to follow-upc | 8 (5.0) | 10 (6.1)
aUSP MODIFIED.
b95% confidence interval of the difference in treatment failure at 6 months (Myfortic–MMF) is (-7.3%, 2.7%).
cLost to follow-up indicates patients who were lost to follow-up without prior biopsy-proven acute rejection, graft loss, or death.
dLost to follow-up indicates patients who were lost to follow-up without prior graft loss or death (8 Myfortic patients and 12 MMF patients).
e95% confidence interval of the difference in treatment failure at 12 months (Myfortic–MMF) is (-11.2%, 1.8%).

16 HOW SUPPLIED/STORAGE AND HANDLING

180 mg tablet: Lime-green, film-coated round tablet with bevelled edges and the imprint (debossing) “C” on one side, containing 180 mg mycophenolic acid (MPA) as mycophenolate sodium.

Bottles of 120…………………………………………………………………NDC 0078-0385-66

360 mg tablet: Pale orange-red, film-coated ovaloid tablet with imprint (debossing) “CT” on one side, containing 360 mg mycophenolic acid (MPA) as mycophenolate sodium.

Bottles of 120…………………………………………………………………NDC 0078-0386-66

Storage

Store at 20°C to 25°C (68°F to 77°F); excursions permitted between 15°C and 30°C (59°F and 86°F) [see USP Controlled Room Temperature]. Protect from moisture. Dispense in a tight container (USP).

Handling

Keep out of reach and sight of children. Myfortic tablets should not be crushed or cut in order to maintain the integrity of the enteric coating [see Dosage and Administration (2.3)].

Teratogenic effects have been observed with mycophenolate sodium [see Warnings and Precautions (5.1)]. If for any reason the Myfortic tablets must be crushed, avoid inhalation of the powder, or direct contact of the powder, with skin or mucous membranes.

17 PATIENT COUNSELING INFORMATION

Advise the patient to read the FDA-approved patient labeling (Medication Guide).

Embryo-Fetal Toxicity

Pregnancy loss and malformations

- Inform pregnant women and females of reproductive potential that use of Myfortic in pregnancy is associated with an increased risk of first trimester pregnancy loss and an increased risk of congenital malformations. Advise patients that they must use an acceptable form of contraception [see Warnings and Precautions (5.1), Use in Specific Populations (8.1, 8.3)].
- Encourage pregnant women to enroll in the Mycophenolate Pregnancy Registry (1-800-617-8191). This registry monitors pregnancy outcomes in women exposed to mycophenolate [see Use in Specific Populations (8.1)].

Contraception

- Discuss pregnancy testing, pregnancy prevention and planning with females of reproductive potential [see Use in Specific Populations (8.3)].
- Females of reproductive potential must use acceptable form of birth control during the entire Myfortic therapy and for 6 weeks after stopping Myfortic, unless the patient chooses to avoid heterosexual sexual intercourse completely (abstinence). Myfortic may reduce effectiveness of oral contraceptives. Use of additional barrier contraceptive methods is recommended [see Use in Specific Populations (8.3)].
- For patients who are considering pregnancy, discuss appropriate alternative immunosuppressants with less potential for embryo-fetal toxicity. Risks and benefits of Myfortic should be discussed with the patient [see Use in Specific Populations (8.3)].
- Advise sexually active male patients and/or their partners to use effective contraception during the treatment of the male patient and for at least 90 days after cessation of treatment. This recommendation is based on findings of animal studies.

Development of Lymphoma and Other Malignancies

- Inform patients they are at increased risk of developing lymphomas and other malignancies, particularly of the skin, due to immunosuppression [see Warnings and Precautions (5.3)].
- Advise patients to limit exposure to sunlight and ultraviolet (UV) light by wearing protective clothing and use a broad-spectrum sunscreen with a high protection factor [see Warnings and Precautions (5.3)].

Increased Risk of Infection

Inform patients they are at increased risk of developing a variety of infections, including opportunistic infections, due to immunosuppression and to contact their physician if they develop any symptoms of infection as explained in the Medication Guide [see Warnings and Precautions (5.4, 5.5)].

Blood Dyscrasias

Inform patients they are at increased risk for developing blood dyscrasias (e.g., neutropenia or anemia) and to immediately contact their healthcare provider if they experience any evidence of infection, unexpected bruising, bleeding, or any other manifestation of bone marrow suppression [see Warnings and Precautions (5.6)].

Gastrointestinal Tract Complications

Inform patients that Myfortic can cause gastrointestinal tract complications, including bleeding, intestinal perforations, and gastric or duodenal ulcers. Advise the patient to contact their healthcare provider if they have symptoms of gastrointestinal bleeding or sudden onset or persistent abdominal pain [see Warnings and Precautions (5.7)].

Acute Inflammatory Syndrome

Inform patients that acute inflammatory reactions have been reported in some patients who received mycophenolate products. Some reactions were severe, requiring hospitalization. Advise patients to contact their physician if they develop fever, joint stiffness, joint pain or muscle pains [see Warnings and Precautions (5.8)].

Hypersensitivity Reactions

Inform patients of the potential risk of hypersensitivity reactions. Advise patients to stop taking Myfortic and seek immediate medical attention if signs or symptoms of a hypersensitivity reaction occur (such as swelling of face, lips, tongue, or throat; difficulty breathing or swallowing) [see Warnings and Precautions (5.9)].

Immunizations

Inform patients that Myfortic can interfere with the usual response to immunizations and that they should avoid live vaccines. Before seeking vaccines on their own, advise patients to discuss first with their physician [see Warnings and Precautions (5.10)].

Administration Instructions

Advise patients to swallow Myfortic tablets whole, and not to crush, chew, or cut the tablets. Inform patients to take Myfortic on an empty stomach, 1 hour before or 2 hours after food intake.

Blood Donation

Advise patients not to donate blood during therapy and for at least 6 weeks following discontinuation of Myfortic [see Warnings and Precautions (5.12)].

Semen Donation

Advise males of childbearing potential not to donate semen during therapy and for 90 days following discontinuation of Myfortic [see Warnings and Precautions (5.13)].

Drug Interactions

Patients should be advised to report to their doctor the use of any other medications while taking Myfortic. The simultaneous administration of any of the following drugs with Myfortic may result in clinically significant adverse reactions:

- Antacids with magnesium and aluminum hydroxides [see Drug Interactions (7.1)], Clinical Pharmacology (12.3)]
- Azathioprine [see Drug Interactions (7.2)]
- Cholestyramine [see Drug Interactions (7.3), Clinical Pharmacology (12.3)]
- Hormonal Contraceptives (e.g., birth control pill, transdermal patch, vaginal ring, injection, and implant) [see Warnings and Precautions (5.2), Drug Interactions (7.8)]

Distributed by:
Novartis Pharmaceuticals Corporation
East Hanover, New Jersey 07936

T2025-35

MEDICATION GUIDE
MYFORTIC® (my-for-tic)
(mycophenolic acid)
delayed-release tablets

Read the Medication Guide that comes with Myfortic before you start taking it and each time you get a refill. There may be new information. This Medication Guide does not take the place of talking with your healthcare provider about your medical condition or treatment. If you have any questions about Myfortic, ask your doctor.
What is the most important information I should know about Myfortic?
Myfortic can cause serious side effects, including:

- Increased risk of loss of pregnancy (miscarriage) and higher risk of birth defects. Females who take Myfortic during pregnancy, have a higher risk of miscarriage during the first 3 months (first trimester), and a higher risk that their baby will be born with birth defects.
  - If you are a female who can become pregnant:
    - your doctor must talk with you about acceptable birth control methods (contraceptive counseling) while taking Myfortic.
    - you should have a pregnancy test immediately before starting Myfortic and another pregnancy test 8 to 10 days later. Pregnancy tests should be repeated during routine follow-up visits with your doctor. Talk to your doctor about the results of all of your pregnancy tests.
    - you must use acceptable birth control during your entire Myfortic therapy and for 6 weeks after stopping Myfortic, unless at any time you choose to avoid sexual intercourse (abstinence) with a man completely. Myfortic decreases blood levels of the hormones in birth control pills that you take by mouth. Birth control pills may not work as well while you take Myfortic and you could become pregnant. If you decide to take birth control pills while using Myfortic, you must also use another form of birth control. Talk to your doctor about other birth control methods that can be used while taking Myfortic.
  - If you are a sexually active male whose female partner can become pregnant, use effective contraception while you are taking Myfortic and for at least 90 days after stopping Myfortic.
- If you plan to become pregnant, talk with your doctor. Your doctor will decide if other medicines to prevent rejection may be right for you.
- If you become pregnant while taking Myfortic, do not stop taking Myfortic. Call your doctor right away. You and your doctor may decide that other medicines to prevent rejection may be right for you. You and your doctor should report your pregnancy to Mycophenolate Pregnancy Registry (1-800-617-8191)
  The purpose of this registry is to gather information about the health of your baby.

- Increased risk of getting serious infections. Myfortic weakens the body’s immune system and affects your ability to fight infections. Serious infections can happen with Myfortic and can lead to death. These serious infections can include:
  - Viral infections. Certain viruses can live in your body and cause active infections when your immune system is weak. Viral infections that can happen with Myfortic include:
    - Shingles, other herpes infections, and cytomegalovirus (CMV). CMV can cause serious tissue and blood infections.
    - BK virus. BK virus can affect how your kidney works and cause your transplanted kidney to fail.
    - Hepatitis B and C viruses. Hepatitis viruses can affect how your liver works. Talk to your doctor about how hepatitis viruses may affect you.
    - COVID-19
  - A brain infection called Progressive Multifocal Leukoencephalopathy (PML). In some patients Myfortic may cause an infection of the brain that may cause death. You are at risk for this brain infection because you have a weakened immune system. You should tell your healthcare provider right away if you have any of the following symptoms:
    - Weakness on one side of the body
    - You do not care about things that you usually care about (apathy)
    - You are confused or have problems thinking
    - You cannot control your muscles
  - Fungal infections. Yeast and other types of fungal infections can happen with Myfortic and cause serious tissue and blood infections. See “What are the possible side effects of Myfortic?”

Call your doctor right away if you have any of these signs and symptoms of infection:

- Temperature of 100.5°F or greater
- Cold symptoms, such as a runny nose or sore throat
- Flu symptoms, such as an upset stomach, stomach pain, vomiting, or diarrhea
- Earache or headache
- Pain during urination or you need to urinate often
- White patches in the mouth or throat
- Unexpected bruising or bleeding
- Cuts, scrapes, or incisions that are red, warm, and oozing pus

- Increased risk of getting certain cancers. People who take Myfortic have a higher risk of getting lymphoma, and other cancers, especially skin cancer. Tell your doctor if you have:
  - unexplained fever, tiredness that does not go away, weight loss, or lymph node swelling
  - a brown or black skin lesion with uneven borders, or one part of the lesion does not look like other parts
  - a change in the size or color of a mole
  - a new skin lesion or bump
  - any other changes to your health

See the section “What are the possible side effects of Myfortic?” for other serious side effects.

What is Myfortic?
Myfortic is a prescription medicine given to prevent rejection (antirejection medicine) in people who have received a kidney transplant. Rejection is when the body’s immune system senses the new organ as “foreign” and attacks it.
Myfortic is used with other medicines containing cyclosporine (Sandimmune®, Gengraf®, and Neoral®) and corticosteroids.
Myfortic can be used to prevent rejection in children who are 5 years or older and are stable after having a kidney transplant. It is not known if Myfortic is safe and works in children younger than 5 years. It is not known how Myfortic works in children who have just received a new kidney transplant.

Who should not take Myfortic?
Do not take Myfortic if you have a history of allergic reactions to mycophenolic acid (MPA), mycophenolate sodium, mycophenolate mofetil, or any of the ingredients in Myfortic. See the end of this Medication Guide for a complete list of ingredients in Myfortic.

What should I tell my doctor before I start taking Myfortic?
Tell your healthcare provider about all of your medical conditions, including if you:

- have any digestive problems, such as ulcers
- plan to receive any vaccines. You should not receive live vaccines while you take Myfortic. Some vaccines may not work as well during treatment with Myfortic.
- have Lesch-Nyhan or Kelley-Seegmiller syndrome or another rare inherited deficiency of hypoxanthine-guanine phosphoribosyl-transferase (HGPRT). You should not take Myfortic if you have one of these disorders.
- are pregnant or planning to become pregnant. See “What is the most important information I should know about Myfortic?”
- are breastfeeding or plan to breastfeed. It is not known if Myfortic passes into breast milk. You and your doctor will decide if you will breastfeed while taking Myfortic.

Tell your doctor about all the medicines you take, including prescription and nonprescription medicines, vitamins, and herbal supplements.

Some medicines may affect the way Myfortic works and Myfortic may affect how some medicines work. Especially tell your doctor if you take:

- birth control pills (oral contraceptives). See “What is the most important information I should know about Myfortic?”
- antacids that contain aluminum or magnesium. Myfortic and antacids should not be taken at the same time.
- acyclovir (Zovirax®), Ganciclovir (Cytovene® IV, Valcyte®)
- azathioprine (Azasan®, Imuran®)
- cholestyramine (Questran® Light, Questran®, Locholest Light, Prevalite®)

Know the medicines you take. Keep a list of your medicines with you to show your healthcare provider and pharmacist when you get a new medicine. Do not take any new medicine without talking to your doctor.

How should I take Myfortic?

- Take Myfortic exactly as prescribed. Your healthcare provider will tell you how much Myfortic to take.
- Do not stop taking or change your dose of Myfortic without talking to your healthcare provider.
- Take Myfortic on an empty stomach, either 1 hour before or 2 hours after a meal.
- Swallow Myfortic whole. Do not crush, chew, or cut Myfortic. The Myfortic tablets have a coating so that the medicine will pass through your stomach and dissolve in your intestine.
  - If you forget to take Myfortic, take it as soon as you remember and then take your next dose at its regular time. If it is almost time for your next dose, skip the missed dose. Do not take two doses at the same time. Call your doctor or pharmacist if you are not sure what to do.
  - If you take more than the prescribed dose of Myfortic, call your doctor right away.
  - Do not change (substitute) between using Myfortic delayed-release tablets and mycophenolate mofetil tablets, capsules, or oral suspension for one another unless your healthcare provider tells you to. These medicines are absorbed differently. This may affect the amount of medicine in your blood.
  - Be sure to keep all appointments at your transplant clinic. During these visits, your doctor may perform regular blood tests.

What should I avoid while taking Myfortic?

- Avoid pregnancy. See “What is the most important information I should know about Myfortic?”
- Limit the amount of time you spend in sunlight. Avoid using tanning beds and sunlamps. People who take Myfortic have a higher risk of getting skin cancer. See “What is the most important information I should know about Myfortic?” Wear protective clothing when you are in the sun and use a broad-spectrum sunscreen with a high sun protection factor (SPF 30 and above). This is especially important if your skin is fair (light colored) or you have a family history of skin cancer.
- You should not donate blood while taking Myfortic and for at least 6 weeks after stopping Myfortic.
- You should not donate sperm while taking Myfortic and for 90 days after stopping Myfortic.
- Elderly patients 65 years of age or older may have more side effects with Myfortic because of a weaker immune system.

What are the possible side effects of Myfortic?
Myfortic can cause serious side effects, including.
See "What is the most important information I should know about Myfortic?"

- Stomach problems. Stomach and intestinal bleeding can happen in people who take Myfortic. Bleeding can be severe and you may have to be hospitalized for treatment.
- Inflammatory reactions. Some people taking Myfortic may have an inflammatory reaction with fever, joint stiffness, joint pain, and muscle pain. Some of these reactions may require hospitalization. This reaction could happen within weeks to months after you start treatment with Myfortic or if your dose is increased. Call your doctor right away if you experience these symptoms.
- Allergic (hypersensitivity) reactions. Allergic reactions, including a severe allergic reaction called anaphylaxis, can happen after taking Myfortic. Stop taking Myfortic and get emergency medical help right away if you have any of the following symptoms of an allergic reaction:

○ swelling of the face, lips, tongue, or throat
○ rash, hives, or itching
○ fainting, dizziness, feeling lightheaded

○ trouble breathing or swallowing
○ fast heartbeat
○ chest pain

The most common side effects of taking Myfortic include:

- low blood cell counts
  - red blood cells
  - white blood cells
  - platelets
- constipation
- nausea
- diarrhea
- vomiting
- urinary tract infections
- stomach upset

Your healthcare provider will do blood tests before you start taking Myfortic and during treatment with Myfortic to check your blood cell counts. Tell your healthcare provider right away if you have any signs of infection (see “What is the most important information I should know about Myfortic?”), or any unexpected bruising or bleeding. Also, tell your healthcare provider if you have unusual tiredness, dizziness, or fainting.

These are not all the possible side effects of Myfortic. Your healthcare provider may be able to help you manage these side effects.

Call your doctor for medical advice about side effects. You may report side effects to

- FDA MedWatch at 1-800-FDA-1088 or
- Novartis Drug Safety at 1-888-NOW-NOVA (1-888-669-6682).

How should I store Myfortic?

- Store Myfortic tablets at room temperature, 59°F to 86°F (15°C to 30°C). Myfortic does not need to be refrigerated.
- Keep the container tightly closed. Store Myfortic in a dry place.
- Keep Myfortic and all medicines out of the reach of children.

General information about Myfortic.

Medicines are sometimes prescribed for purposes other than those listed in a Medication Guide. Do not use Myfortic for a condition for which it was not prescribed. Do not give Myfortic to other people, even if they have the same symptoms you have. It may harm them.

This Medication Guide summarizes the most important information about Myfortic. If you would like more information, talk with your doctor. You can ask your doctor or pharmacist for information about Myfortic that is written for healthcare professionals. You can also call 1-888-669-6682 or visit the Myfortic website at www.myfortic.com.

What are the ingredients in Myfortic?

Active ingredient: mycophenolic acid (as mycophenolate sodium)

Inactive ingredients: colloidal silicon dioxide, crospovidone, lactose anhydrous, magnesium stearate, povidone (K-30), and starch. The enteric coating of the tablet consists of hypromellose phthalate, titanium dioxide, iron oxide yellow, and indigotine (for the 180-mg tablet) or iron oxide red (for the 360-mg tablet)

Sandimmune and Neoral are registered trademarks of Novartis Pharmaceuticals Corporation.

Any other trademarks in this document are the property of their respective owners.

Distributed by:
Novartis Pharmaceuticals Corporation
East Hanover, New Jersey 07936

© Novartis

This Medication Guide has been approved by the U.S. Food and Drug Administration.

Revised: June 2025

T2025-36

PRINCIPAL DISPLAY PANEL

NOVARTIS

NDC 0078-0385-66

Myfortic®

(mycophenolic acid*)

delayed-release tablets

*as mycophenolate sodium

Dispense the accompanying Medication Guide to each patient.

120 Tablets

180 mg

Rx only

PRINCIPAL DISPLAY PANEL

NOVARTIS

NDC 0078-0386-66

Myfortic®

(mycophenolic acid*)

delayed-release tablets

*as mycophenolate sodium

Dispense the accompanying Medication Guide to each patient.

120 Tablets

360 mg

Rx only